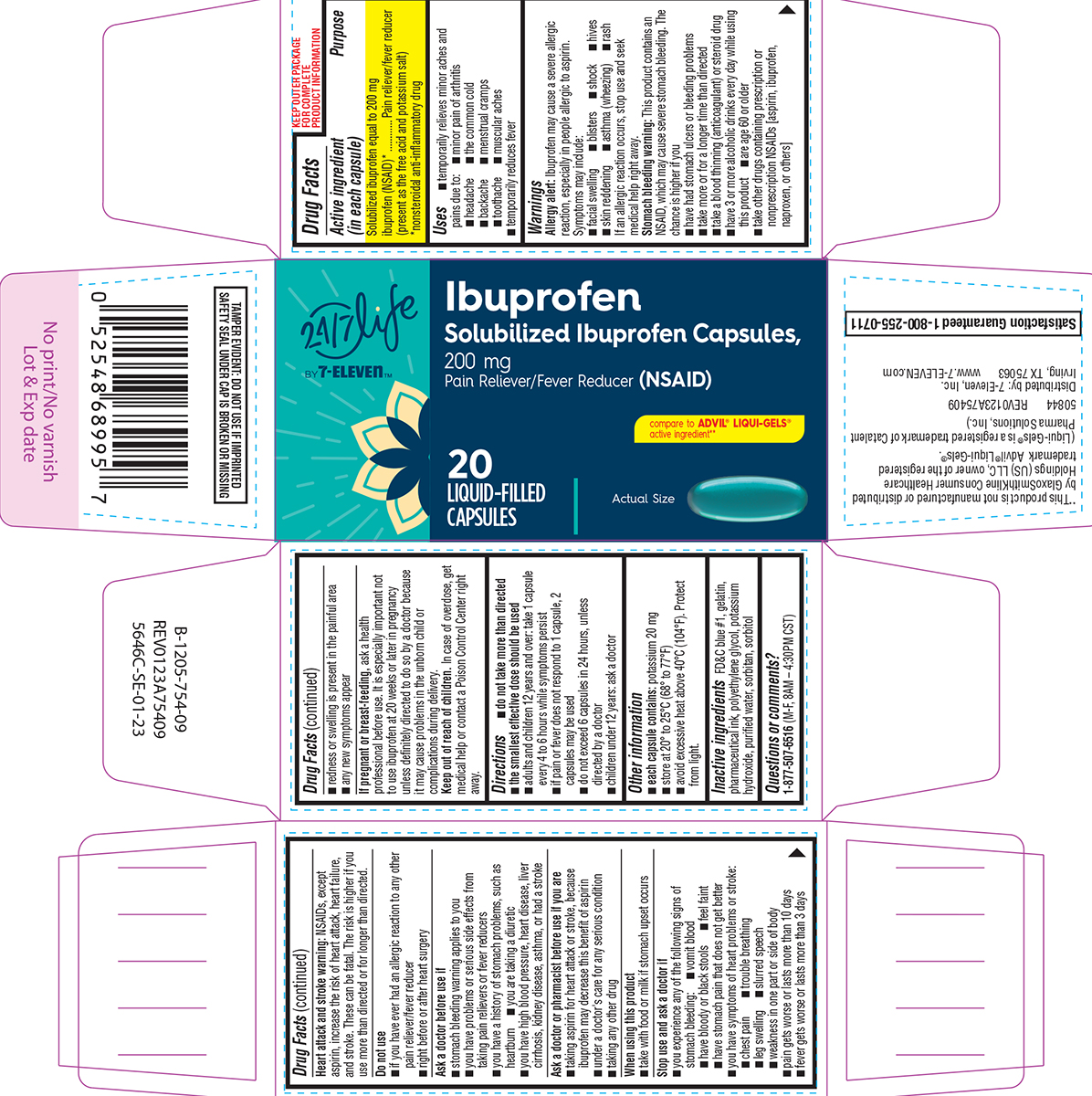 DRUG LABEL: Ibuprofen
NDC: 50844-754 | Form: CAPSULE, LIQUID FILLED
Manufacturer: L.N.K. International, Inc.
Category: otc | Type: HUMAN OTC DRUG LABEL
Date: 20260202

ACTIVE INGREDIENTS: IBUPROFEN 200 mg/1 1
INACTIVE INGREDIENTS: FD&C BLUE NO. 1; GELATIN, UNSPECIFIED; POLYETHYLENE GLYCOL, UNSPECIFIED; POTASSIUM HYDROXIDE; WATER; SORBITAN; SORBITOL

Convenience Valet 44-754

Active ingredient (in each capsule)

Solubilized ibuprofen equal to 200 mg ibuprofen (NSAID)*
(present as the free acid and potassium salt)
*nonsteroidal anti-inflammatory drug

Purpose

Pain reliever/fever reducer

Uses

- temporarily relieves minor aches and pains due to:
  - minor pain of arthritis
  - headache
  - the common cold
  - backache
  - menstrual cramps
  - toothache
  - muscular aches
- temporarily reduces fever

Warnings

Allergy alert: Ibuprofen may cause a severe allergic reaction, especially in people allergic to aspirin. Symptoms may include:

- facial swelling
- blisters
- shock
- hives
- skin reddening
- asthma (wheezing)
- rash

If an allergic reaction occurs, stop use and seek medical help right away.

Stomach bleeding warning: This product contains an NSAID, which may cause severe stomach bleeding. The chance is higher if you

- have had stomach ulcers or bleeding problems
- take more or for a longer time than directed
- take a blood thinning (anticoagulant) or steroid drug
- have 3 or more alcoholic drinks every day while using this product
- are age 60 or older
- take other drugs containing prescription or nonprescription NSAIDs [aspirin, ibuprofen, naproxen, or others]

Heart attack and stroke warning: NSAIDs, except aspirin, increase the risk of heart attack, heart failure, and stroke. These can be fatal. The risk is higher if you use more than directed or for longer than directed.

Do not use

- if you have ever had an allergic reaction to any other pain reliever/fever reducer
- right before or after heart surgery

Ask a doctor before use if

- stomach bleeding warning applies to you
- you have problems or serious side effects from taking pain relievers or fever reducers
- you have a history of stomach problems, such as heartburn
- you are taking a diuretic
- you have high blood pressure, heart disease, liver cirrhosis, kidney disease, asthma, or had a stroke

Ask a doctor or pharmacist before use if you are

- taking aspirin for heart attack or stroke, because ibuprofen may decrease this benefit of aspirin
- under a doctor's care for any serious condition
- taking any other drug

When using this product

- take with food or milk if stomach upset occurs

Stop use and ask a doctor if

- you experience any of the following signs of stomach bleeding:
  - vomit blood
  - have bloody or black stools
  - feel faint
  - have stomach pain that does not get better
- you have symptoms of heart problems or stroke:
  - chest pain
  - trouble breathing
  - leg swelling
  - slurred speech
  - weakness in one part or side of body
- pain gets worse or lasts more than 10 days
- fever gets worse or lasts more than 3 days
- redness or swelling is present in the painful area
- any new symptoms appear

If pregnant or breast-feeding,

ask a health professional before use. It is especially important not to use ibuprofen at 20 weeks or later in pregnancy unless definitely directed to do so by a doctor because it may cause problems in the unborn child or complications during delivery.

Keep out of reach of children.

In case of overdose, get medical help or contact a Poison Control Center right away.

Directions

- do not take more than directed
- the smallest effective dose should be used
- adults and children 12 years and over: take 1 capsule every 4 to 6 hours while symptoms persist
- if pain or fever does not respond to 1 capsule, 2 capsules may be used
- do not exceed 6 capsules in 24 hours, unless directed by a doctor
- children under 12 years: ask a doctor

Other information

- each capsule contains: potassium 20 mg
- store at 20º to 25°C (68º to 77°F)
- avoid excessive heat above 40°C (104°F). Protect from light.

Inactive ingredients

FD&C blue #1, gelatin, pharmaceutical ink, polyethylene glycol, potassium hydroxide, purified water, sorbitan, sorbitol

Questions or comments?

1-877-507-6516 (M-F, 8AM – 4:30PM CST)

Principal display panel

24/7 life
by 7-Eleven™

Ibuprofen
Solubilized Ibuprofen Capsules,
200 mg
Pain Reliever/Fever Reducer (NSAID)

compare to ADVIL® LIQUI-GELS®
active ingredient**

20
LIQUID-FILLED
CAPSULES

Actual Size

TAMPER EVIDENT: DO NOT USE IF IMPRINTED
SAFETY SEAL UNDER CAP IS BROKEN OR MISSING

**This product is not manufactured or distributed
by GlaxoSmithKline Consumer Healthcare
Holdings (US) LLC, owner of the registered
trademark Advil® Liqui-Gels®.
(Liqui-Gels® is a registered trademark of Catalent
Pharma Solutions, Inc.)

50844 REV0123A75409

Distributed by: 7-Eleven, Inc.
Irving, TX 75063 www.7-ELEVEN.com

Satisfaction Guaranteed 1-800-255-0711

Convenience Valet 44-754